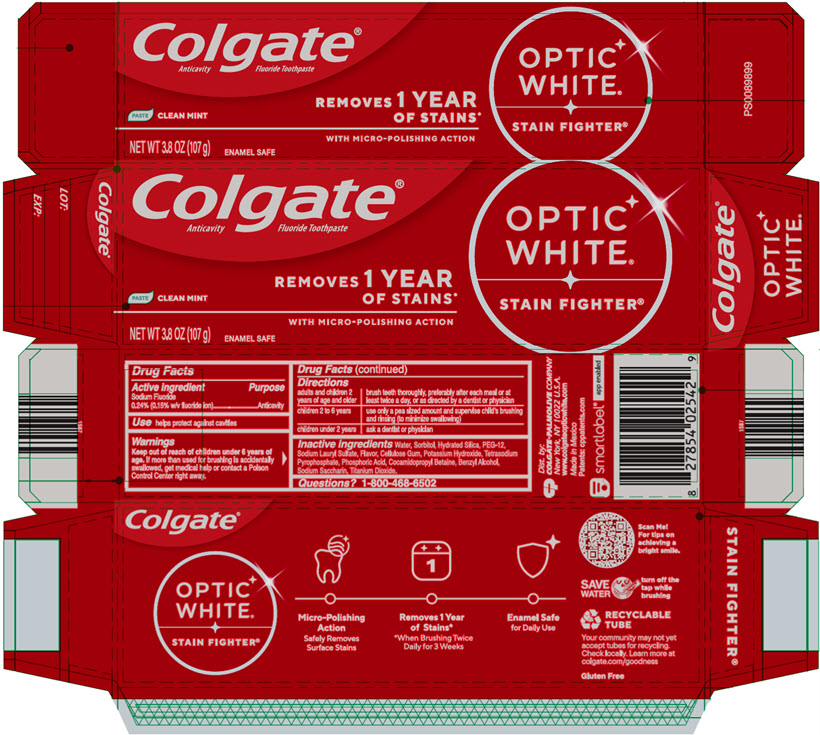 DRUG LABEL: OPTIC WHITE NON-HP STAIN FIGHTER CLEAN MINT
NDC: 35000-793 | Form: PASTE, DENTIFRICE
Manufacturer: Colgate-Palmolive Company
Category: otc | Type: HUMAN OTC DRUG LABEL
Date: 20251107

ACTIVE INGREDIENTS: SODIUM FLUORIDE 1.1 mg/1 g
INACTIVE INGREDIENTS: WATER; SORBITOL 460.9 mg/1 g; HYDRATED SILICA; POLYETHYLENE GLYCOL 600; SODIUM LAURYL SULFATE; CARBOXYMETHYLCELLULOSE; POTASSIUM HYDROXIDE; SODIUM PYROPHOSPHATE; PHOSPHORIC ACID; COCAMIDOPROPYL BETAINE; BENZYL ALCOHOL; SACCHARIN SODIUM; TITANIUM DIOXIDE

OPTIC WHITE® NON-HP STAIN FIGHTER® CLEAN MINT

Drug Facts

Active ingredient

Sodium Fluoride 0.24% (0.15% w/v fluoride ion)

Purpose

Anticavity

Use

helps protect against cavities

Warnings

Keep out of reach of children under 6 years of age. If more than used for brushing is accidentally swallowed, get medical help or contact a Poison Control Center right away.

Directions

adults and children 2 years of age and older | brush teeth thoroughly, preferably after each meal or at least twice a day, or as directed by a dentist or physician
children 2 to 6 years | use only a pea sized amount and supervise child's brushing and rinsing (to minimize swallowing)
children under 2 years | ask a dentist or physician

Inactive ingredients

Water, Sorbitol, Hydrated Silica, PEG-12, Sodium Lauryl Sulfate, Flavor, Cellulose Gum, Potassium Hydroxide, Tetrasodium Pyrophosphate, Phosphoric Acid, Cocamidopropyl Betaine, Benzyl Alcohol, Sodium Saccharin, Titanium Dioxide.

Questions?

1-800-468-6502

Dist. by:
COLGATE-PALMOLIVE COMPANY
New York, NY 10022 U.S.A.

PRINCIPAL DISPLAY PANEL - 107 g Tube Carton

Colgate®

Anticavity Fluoride Toothpaste

PASTE CLEAR MINT

NET WT 3.8 OZ (107 g)

ENAMEL SAFE

REMOVES 1 YEAR
OF STAINS*
WITH MICRO-POLISHING ACTION

OPTIC
WHITE®

STAIN FIGHTER®